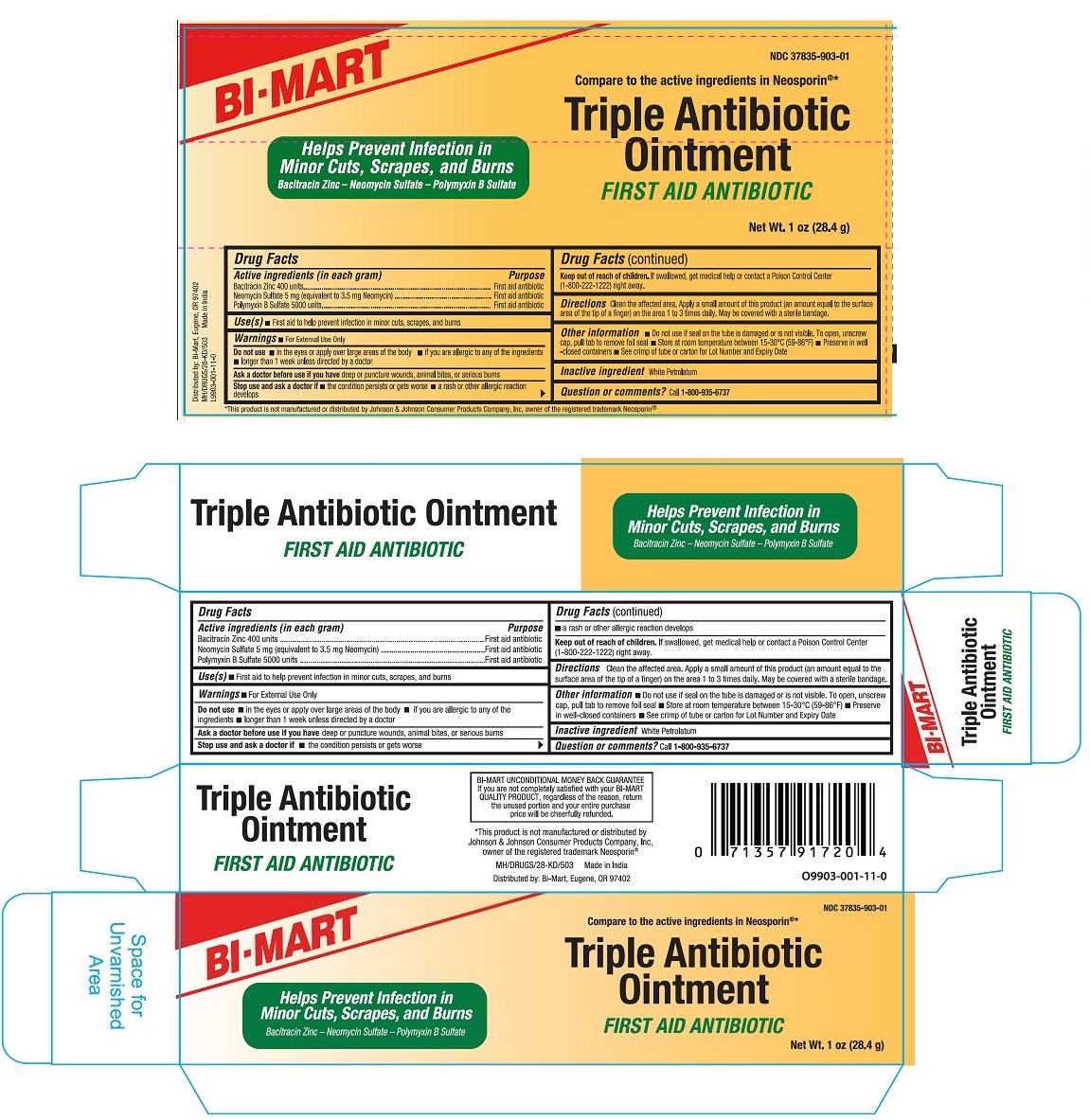 DRUG LABEL: Triple Antibiotic
NDC: 37835-903 | Form: OINTMENT
Manufacturer: Bi-Mart
Category: otc | Type: HUMAN OTC DRUG LABEL
Date: 20241129

ACTIVE INGREDIENTS: BACITRACIN ZINC 400 [USP'U]/1 g; NEOMYCIN SULFATE 5 mg/1 g; POLYMYXIN B SULFATE 5000 [USP'U]/1 g
INACTIVE INGREDIENTS: WHITE PETROLATUM

Bi-Mart (as PLD) - Triple Antibiotic (37835-903)

Active Ingredients (in each gram)

Bacitracin Zinc 400 units

Neomycin Sulfate 5 mg (equivalent to 3.5 mg Neomycin)

Polymyxin B Sulfate 5000 units

Purpose

First aid antibiotic

Use(s)

First aid to help prevent infection in minor cuts, scrapes and burns

Warnings

- For External Use Only

Do not use

- in the eyes or apply over large areas of the body
- if you are allergic to any of the ingredients
- longer than 1 week unless directed by a doctor

Ask a doctor before use if you havedeep or puncture wounds, animal bites, or serious burns

Stop use and ask a doctor if

- the condition persists or gets worse
- a rash or other allergic reaction develops

Keep out of reach of children.If swallowed, get medical help or contact a Poison Control Center (1-800-222-1222) right away.

Directions

Clean the affected area. Apply a small amount of this product (an amount equal to the surface area of th tip of a finger) on the area 1 to 3 times daily. May be covered with a sterile bandage.

Other information

- Do not use if seal on the tube is damaged or is not visible. To open, unscrew cap, pull tab to remove foil seal.
- Store at room temperatue between 15-30°C (59-86°F)
- Preserve in well-closed containers
- See crimp of tube or carton for Lot Number and Expiry Date

Inactive ingredient

White Petrolatum

Questions or comments?

Call 1-800-935-6737

Principal Display Panel

NDC 37835-903-01

Triple Antibiotic Ointment

First aid antibiotic

Compare to the Active Ingredients in Neosporin®*

*This product is not manufactured or distributed by Johnson & Johnson Corporation Products Company, Inc, owner of the registered trademark Neosporin®.

Net. Wt. 1 oz (28.4 g)

Distributed by:

Bi-Mart

Eugene, OR 97402